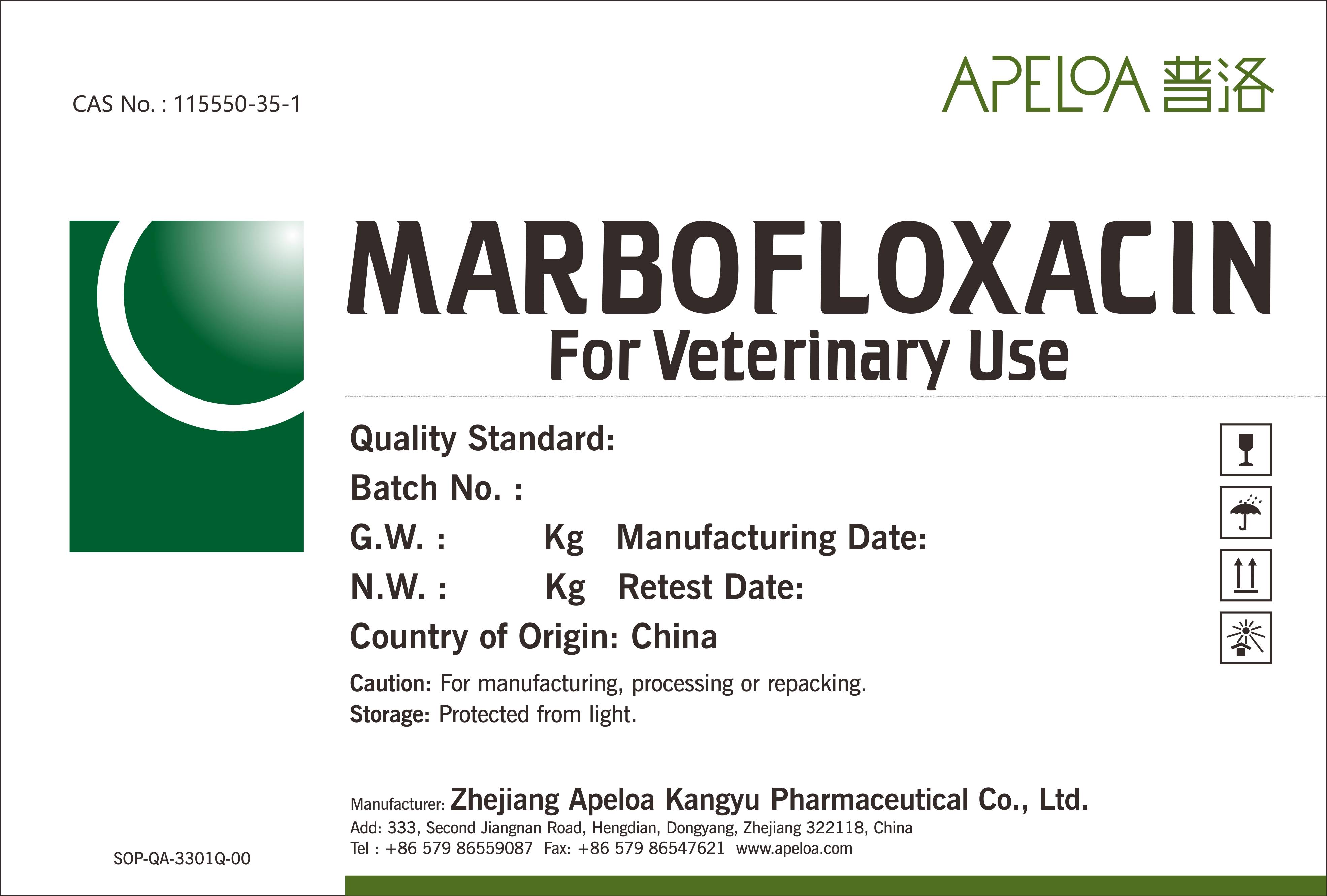 DRUG LABEL: Marbofloxacin
NDC: 66653-010 | Form: POWDER
Manufacturer: Zhejiang Apeloa Kangyu Pharmaceutical Co., Ltd.
Category: other | Type: BULK INGREDIENT - ANIMAL DRUG
Date: 20251225

ACTIVE INGREDIENTS: MARBOFLOXACIN 1 kg/1 kg

Lable of Marbofloxacin